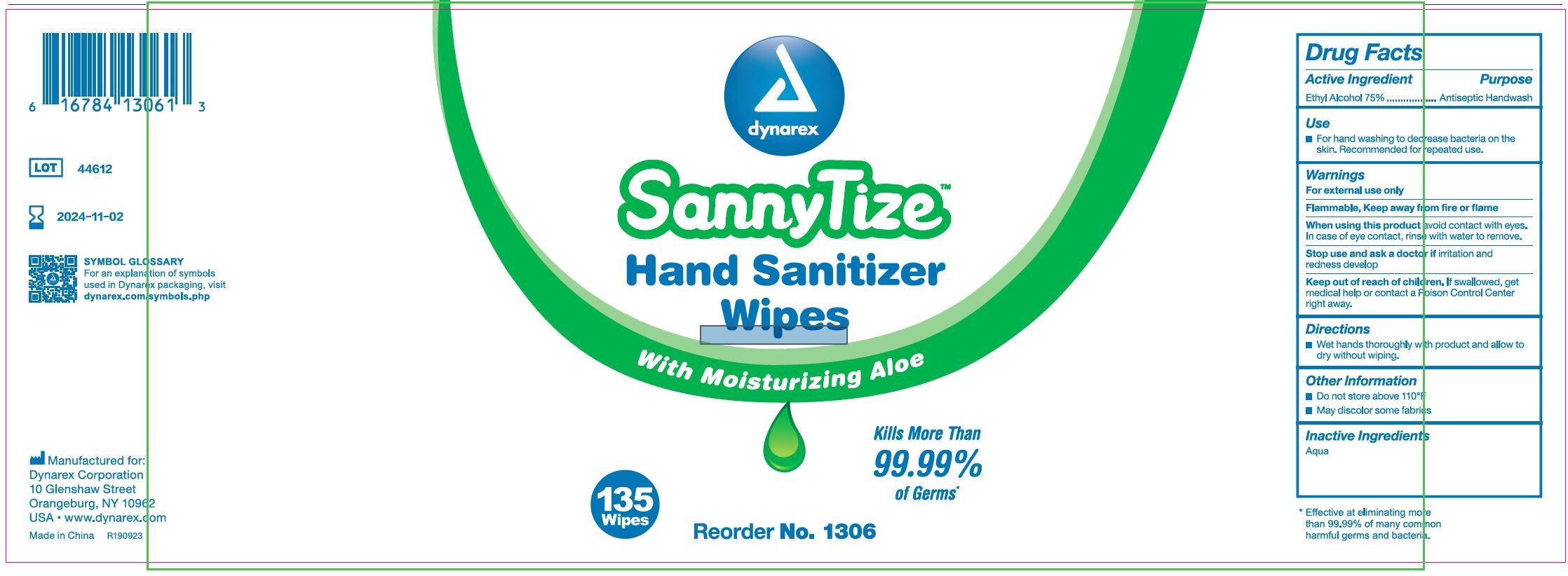 DRUG LABEL: Wet Wipes
NDC: 69821-002 | Form: SWAB
Manufacturer: Zhejiang Qimei Commodity Co.,Ltd.
Category: otc | Type: HUMAN OTC DRUG LABEL
Date: 20221102

ACTIVE INGREDIENTS: ALCOHOL 75 g/100 g
INACTIVE INGREDIENTS: WATER

69821-002 75% Ethyl Alcohol Wet Wipes

Active ingredient

Ethyl Alcohol 75%

Purpose

Antiseptic Handwash

Uses

■ For hand washing to dec rease bacteria on the
skin. Recommended for repeated use.

Warnings

For external use only
Flammable, Keep away from fire or flame
When using this product avoid contact with eyes.
In case of eye contact, rins e with water to remove.
Stop use and ask a doctor if irritation and
redness develop

Keep out of reach of children. If swallowed, get
medical help or contact a Poison Control Center
right away.

Directions

■Wet hands thoroughly wi th product and allow to
dry without wiping.

INACTIVE INGREDIENT

Aqua